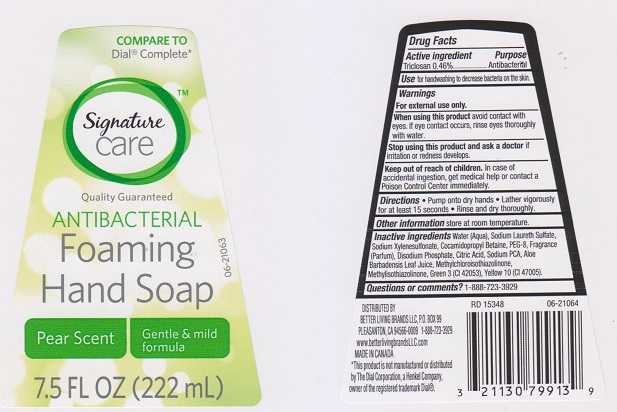 DRUG LABEL: Signature Care Antibacterial Foaming Hand Pear Scent
NDC: 21130-114 | Form: SOAP
Manufacturer: SAFEWAY INC
Category: otc | Type: HUMAN OTC DRUG LABEL
Date: 20160211

ACTIVE INGREDIENTS: TRICLOSAN 4.6 mg/1 mL
INACTIVE INGREDIENTS: WATER; SODIUM LAURETH-3 SULFATE; SODIUM XYLENESULFONATE; COCAMIDOPROPYL BETAINE; POLYETHYLENE GLYCOL 400; SODIUM PHOSPHATE, DIBASIC ANHYDROUS; CITRIC ACID MONOHYDRATE; SODIUM PYRROLIDONE CARBOXYLATE; ALOE VERA LEAF; METHYLCHLOROISOTHIAZOLINONE; METHYLISOTHIAZOLINONE; FD&C GREEN NO. 3; D&C YELLOW NO. 10

DRUG FACTS

Active ingredient

Triclosan 0.46%

Purpose

Antibacterial

Uses

for handwashing to decrease bacteria on the skin.

Warnings

For external use only

When using this product

avoid contact with eyes. If eye contact occurs, rinse eyes thoroughly with water.

Stop using this product and ask a doctor if

irritation or redness develops

Keep out of reach of children.

In case of accidental ingestion, get medical help or contact a Poison Control Center immediately.

Directions

- Pump onto dry hands
- Lather vigorously for at least 15 seconds
- Rinse and dry thoroughly

Other information

store at room temperature.

Inactive ingredients

Water (Aqua), Sodium Laureth Sulfate, Sodium Xylenesulfonate, Cocamidopropyl Betaine, PEG-8, Fragrance (Parfum), Disodium Phosphate, Citric Acid, Sodium PCA, Aloe Barbadensis Leaf Juice, Methylchloroisothiazolinone, Methylisothiazolinone, Green 3 (CI 42053), Yellow 10 (CI 47005).

Questions or comments?

1-888-723-3929